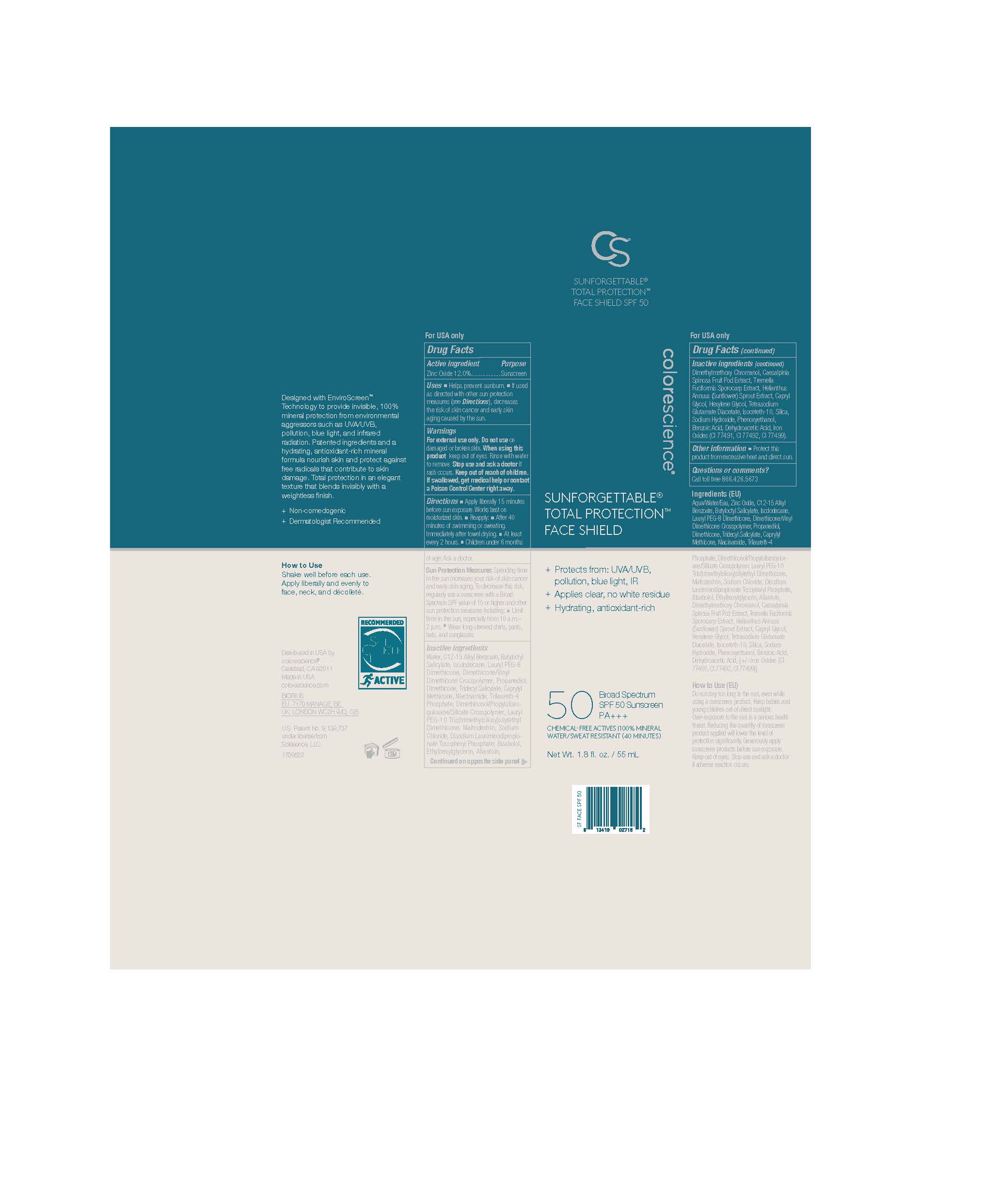 DRUG LABEL: SUNFORGETTABLE TOTAL FACE PROTECTION FACE SHIELD CLASSIC
NDC: 68078-060 | Form: LOTION
Manufacturer: Colorescience
Category: otc | Type: HUMAN OTC DRUG LABEL
Date: 20251015

ACTIVE INGREDIENTS: ZINC OXIDE 135.6 mg/1 mL
INACTIVE INGREDIENTS: TRIDECYL SALICYLATE; DIMETHYLMETHOXY CHROMANOL; .ALPHA.-BISABOLOL, (+)-; SILICON DIOXIDE; DIMETHICONE/VINYL DIMETHICONE CROSSPOLYMER (SOFT PARTICLE); ALLANTOIN; TRILAURETH-4 PHOSPHATE; BUTYLOCTYL SALICYLATE; ISODODECANE; NIACINAMIDE; SODIUM HYDROXIDE; WATER; ETHYLHEXYLGLYCERIN; HEXYLENE GLYCOL; DEHYDROACETIC ACID; DIMETHICONOL/PROPYLSILSESQUIOXANE/SILICATE CROSSPOLYMER (450000000 MW); PROPANEDIOL; TETRASODIUM GLUTAMATE DIACETATE; SODIUM CHLORIDE; PHENOXYETHANOL; TREMELLA FUCIFORMIS FRUITING BODY; MALTODEXTRIN; ALKYL (C12-15) BENZOATE; DISODIUM LAURIMINODIPROPIONATE TOCOPHERYL PHOSPHATES; ISOCETETH-10; DIMETHICONE; CAESALPINIA SPINOSA FRUIT POD; HELIANTHUS ANNUUS SPROUT

SUNFORGETTABLE TOTAL FACE PROTECTION FACE SHIELD CLASSIC